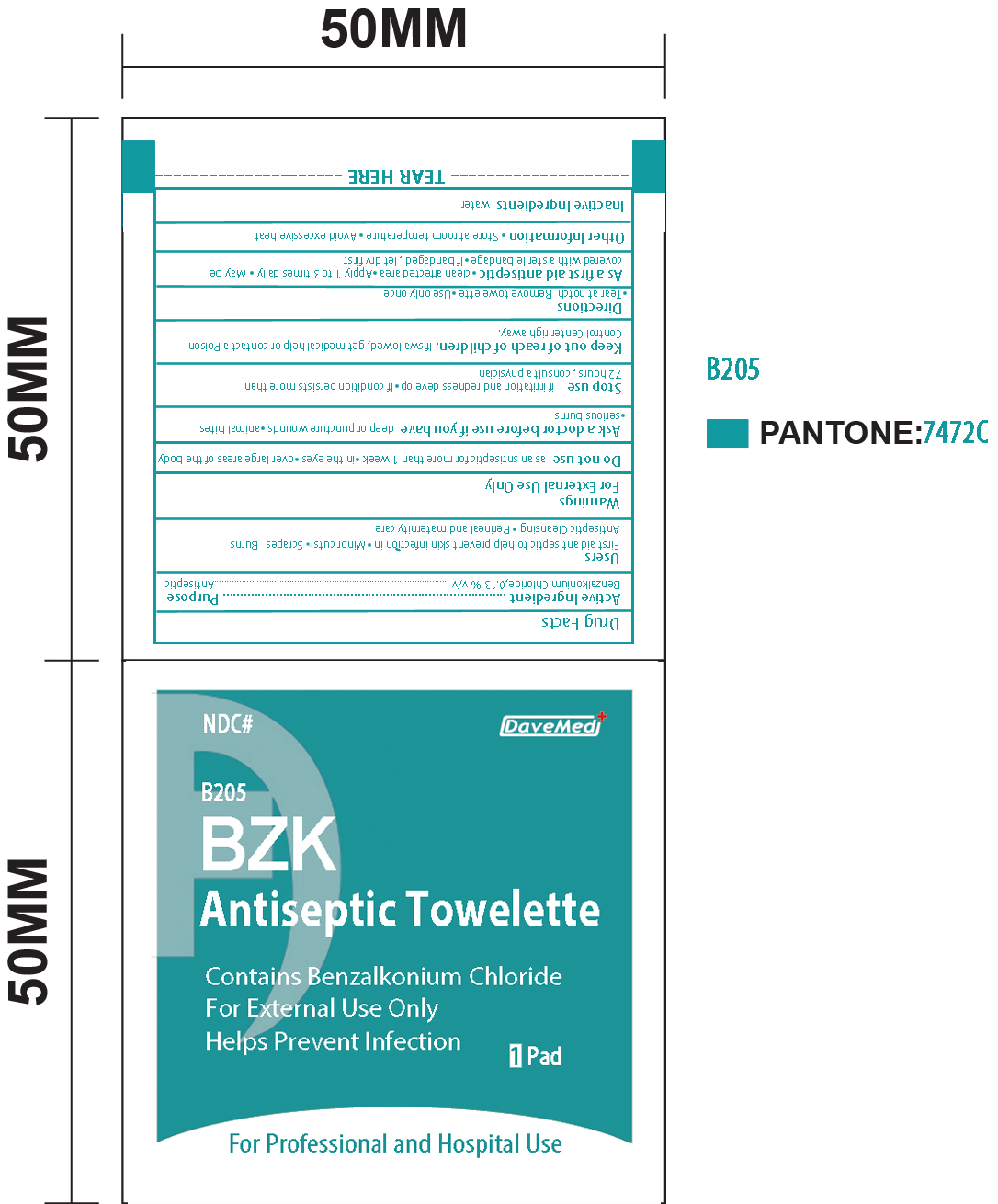 DRUG LABEL: BZK Antiseptic Towelette
NDC: 70897-005 | Form: SWAB
Manufacturer: Davemed Healthcare Co., Ltd
Category: otc | Type: HUMAN OTC DRUG LABEL
Date: 20190124

ACTIVE INGREDIENTS: BENZALKONIUM CHLORIDE 0.0013 mg/1 1
INACTIVE INGREDIENTS: WATER

BZK Antiseptic Towelette

Active Ingredients

Benzalkonium Chloride 0.13% v/v

Purpose

Antiseptic

Use

First aid antiseptic to help prevent skin infection in

- minor cuts
- scrapes, burns, anitiseptic cleansing
- perineal and maternity care

Warnings

For external use only
Do not use:

- as an antiseptic for more than 1 week
- in the eyes
- over large areas of the body

Ask a doctor before use if you have

- deep or puncture wounds
- animal bites
- serious burns

Stop use

- if irritation and redness develop
- if condition persists more than 72 hours, consult a physician

Keep out of reach of children.if swallowed get medical help or contact Poison control Center right away.

Directions

- Tear at notch
- Remove towelette
- Use only once

As a first aid antiseptic

- clean affected area
- apply 1 to 3 times daily
- may be covered with a sterile bandage
- if bandaged, let dry first

Inactive Ingredient

Water

OTHER SAFETY INFORMATION

- Store at room temperature
- Avoid excessive heat